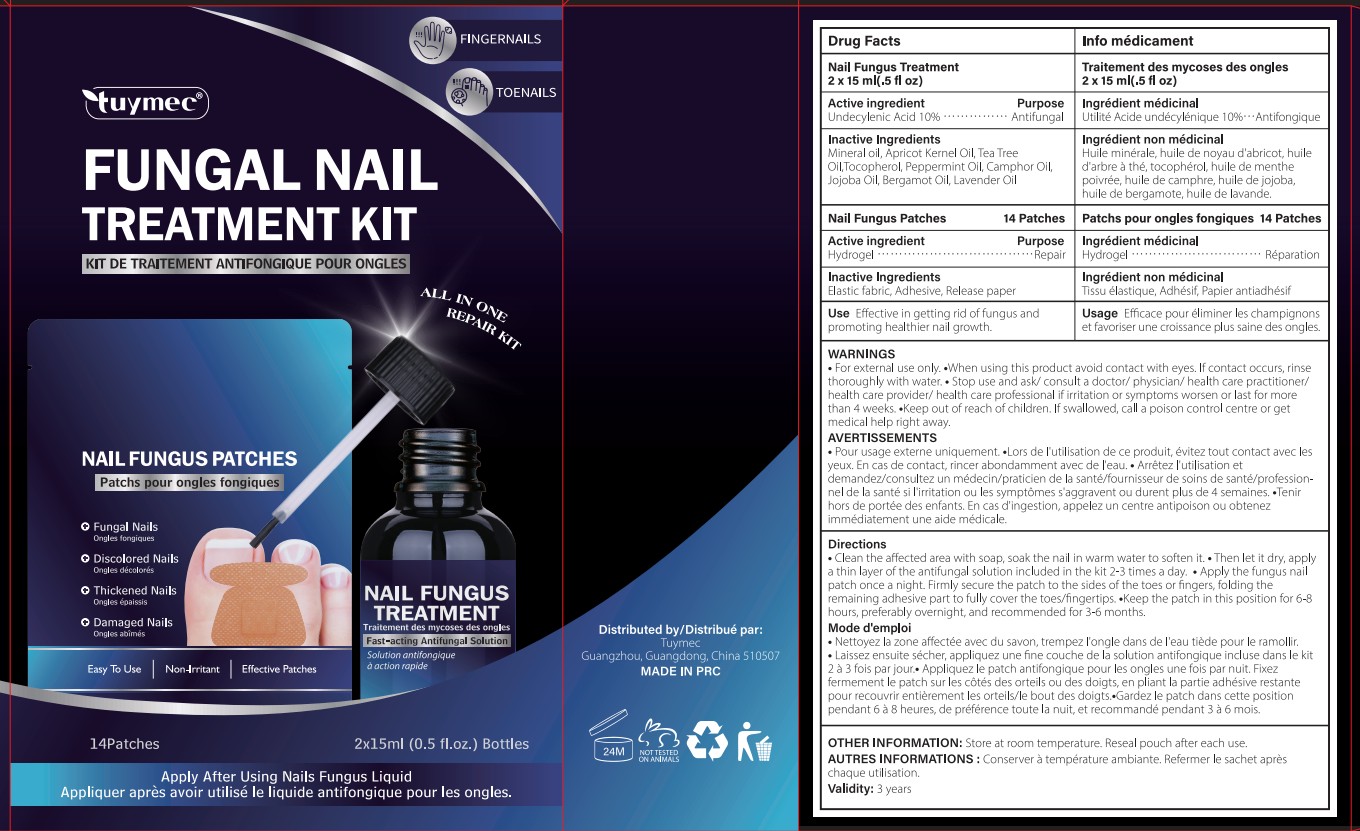 DRUG LABEL: Tuymec FUNGAL NAIL TREATMENT Kit
NDC: 87408-004 | Form: LIQUID
Manufacturer: Guangzhou Jingliang Cosmetics Co., Ltd.
Category: otc | Type: HUMAN OTC DRUG LABEL
Date: 20260211

ACTIVE INGREDIENTS: UNDECYLENIC ACID 10 g/100 mL
INACTIVE INGREDIENTS: PEPPERMINT OIL; CAMPHOR OIL; JOJOBA OIL; APRICOT KERNEL OIL; MINERAL OIL; LAVENDER OIL; BERGAMOT OIL; TOCOPHEROL; TEA TREE OIL

Active Ingredient

Active ingredient: Undecylenic Acid 10%

Ask Doctor

if irritation or symptoms worsen or last for more than 4 weeks.

Do not use

• If you are pregnant or breastfeeding
• your skin is injured or cracked.
• you are under 18 years of age.
• irritation or discomfort occurs.
• you are using other medicines on your nails.

Keep Oot Of Reach Of Children

If swallowed, get medical help or contact a poison control center right away.

Purpose

Antifungal

Stop Use

if irritation or symptoms worsen or last for more than 4 weeks.

When Using

• Do not apply to other parts of the body.
• Avoid making eye contact. In case of accidental eye contact, flush eyes with copious amounts of cold tap water.
• This product may not work for everyone.

Inactive ingredients

Mineral oil, Apricot Kernel Oil, Tea Tree Oil,Tocopherol, Peppermint Oil, Camphor Oil, Jojoba Oil, Bergamot Oil, Lavender Oil

Directions

• Clean the affected area with soap, soak the nail in warm water to soften it.
• Then let it dry, apply a thin layer of the antifungal solution included in the kit 2-3 times a day.
• Apply the fungus nail patch once a night. Firmly secure the patch to the sides of the toes or fingers, folding the remaining adhesive part to fully cover the toes/fingertips.
• Keep the patch in this position for 6-8 hours, preferably overnight, and recommended for 3-6 months.

Warnings

• For external use only.
• When using this product avoid contact with eyes. If contact occurs, rinse thoroughly with water.
• Stop use and ask/ consult a doctor/ physician/ health care practitioner/ health care provider/ health care professional if irritation or symptoms worsen or last for more than 4 weeks.
• Keep out of reach of children. If swallowed, call a poison control centre or get medical help right away.

Uses

Effective in getting rid of fungus and promoting healthier nail growth

PACKAGE LABEL

Product Name: Tuymec FUNGAL NAIL TREATMENT KIT

Net Contents: 2x15ml (0.5 fl.oz.) Bottles